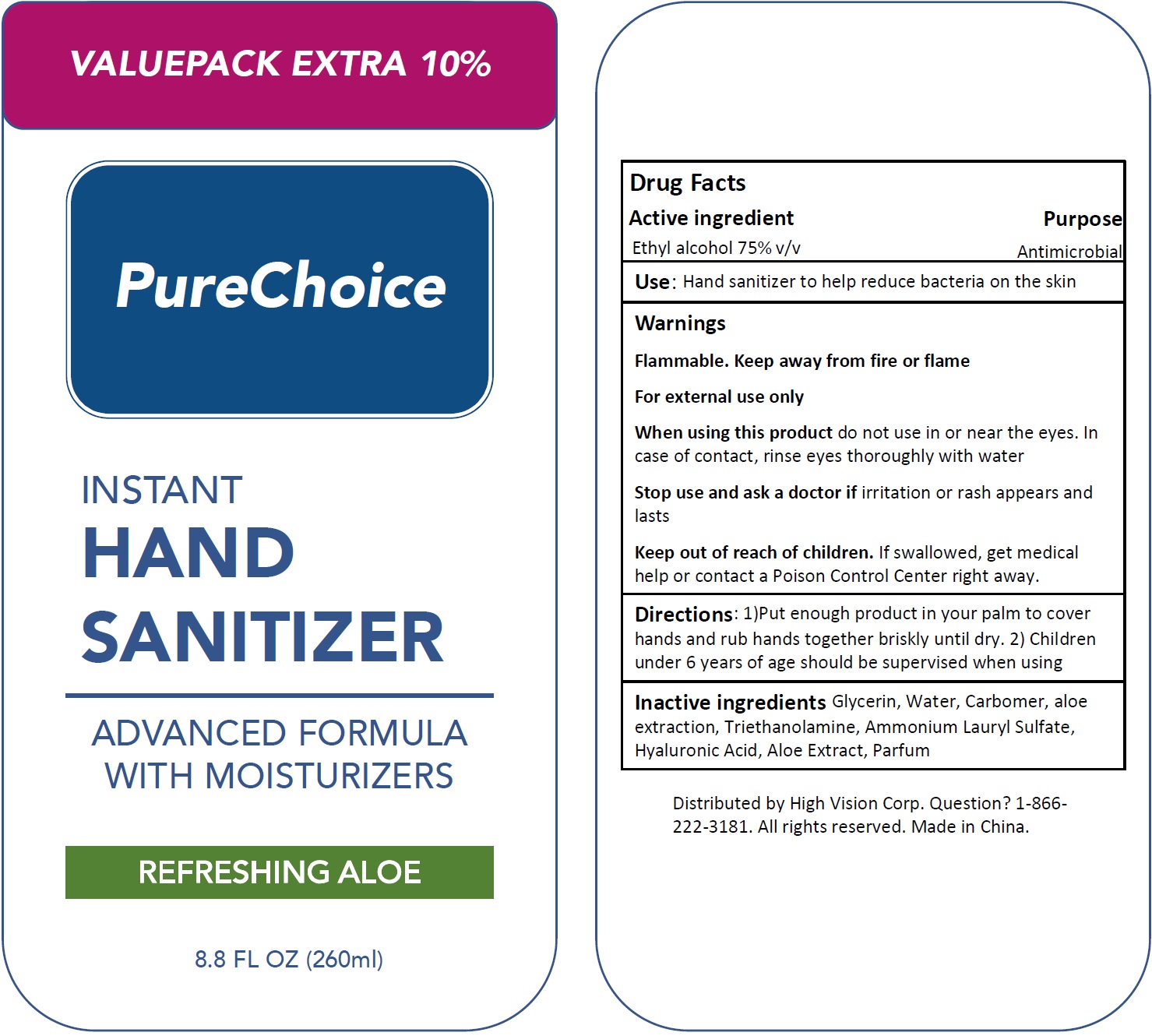 DRUG LABEL: Pure Choice Instant Hand Sanitizer
NDC: 74854-001 | Form: GEL
Manufacturer: Shanghai Medical Instruments Co.,Ltd
Category: otc | Type: HUMAN OTC DRUG LABEL
Date: 20200427

ACTIVE INGREDIENTS: ALCOHOL 0.75 mL/1 mL
INACTIVE INGREDIENTS: GLYCERIN; WATER; CARBOMER HOMOPOLYMER, UNSPECIFIED TYPE; TROLAMINE; AMMONIUM LAURYL SULFATE; HYALURONIC ACID; ALOE

Pure Choice Instant Hand Sanitizer

Active ingredient

Ethyl alcohol 75% v/v

Purpose

Antimicrobial

Use:

Hand sanitizer to help reduce bacteria on the skin

Warnings

Flammable. Keep away from fire or flame
For external use only

When using this product

do not use in or near the eyes. In case of contact, rinse eyes thoroughly with water

Stop use and ask a doctor if

irritation or rash appears and lasts

Keep out of reach of children.

If swallowed, get medical help or contact a Poison Control Center right away.

Directions:

1)Put enough product in your palm to cover hands and rub hands together briskly until dry. 2) Children under 6 years of age should be supervised when using

Inactive ingredients

Glycerin, Water, Carbomer, aloe extraction, Triethanolamine, Ammonium Lauryl Sulfate, Hyaluronic Acid, Aloe Extract, Parfum

QUESTIONS

Question? 1-866-222-3181.